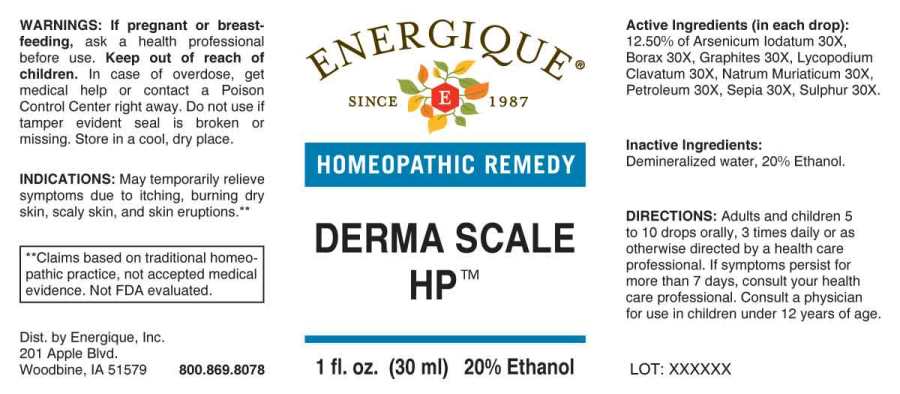 DRUG LABEL: DERMA SCALE HP
NDC: 44911-0566 | Form: LIQUID
Manufacturer: Energique, Inc.
Category: homeopathic | Type: HUMAN OTC DRUG LABEL
Date: 20240123

ACTIVE INGREDIENTS: ARSENIC TRIIODIDE 30 [hp_X]/1 mL; SODIUM BORATE 30 [hp_X]/1 mL; GRAPHITE 30 [hp_X]/1 mL; LYCOPODIUM CLAVATUM SPORE 30 [hp_X]/1 mL; SODIUM CHLORIDE 30 [hp_X]/1 mL; KEROSENE 30 [hp_X]/1 mL; SEPIA OFFICINALIS JUICE 30 [hp_X]/1 mL; SULFUR 30 [hp_X]/1 mL
INACTIVE INGREDIENTS: WATER; ALCOHOL

DRUG FACTS:

ACTIVE INGREDIENTS:

(in each drop): 12.50% of Arsenicum Iodatum 30X, Borax 30X, Graphites 30X, Lycopodium Clavatum 30X, Natrum Muriaticum 30X, Petroleum 30X, Sepia 30X, Sulphur 30X.

INDICATIONS:

May temporarily relieve symptoms itching, burning dry skin, scaly skin, and skin eruptions.**

**Claims based on traditional homeopathic practice, not accepted medical evidence. Not FDA evaluated.

WARNINGS:

If pregnant or breast-feeding, ask a health professional before use.

Keep out of reach of children. In case of overdose, get medical help or contact a Poison Control Center right away.

Do not use if tamper evident seal is broken or missing. Store in a cool, dry place.

KEEP OUT OF REACH OF CHILDREN:

In case of overdose, get medical help or contact a Poison Control Center right away.

DIRECTIONS:

Adults and children 5 to 10 drops orally, 3 times daily or as otherwise directed by a health care professional. If symptoms persist for more than 7 days, consult your health care professional. Consult a physician for use in children under 12 years of age.

INDICATIONS:

For temporary relief of symptoms due to psoriasis and skin eruptions.**

**Claims based on traditional homeopathic practice, not accepted medical evidence. Not FDA evaluated.

INACTIVE INGREDIENTS:

Demineralized water, 20% Ethanol

QUESTIONS:

Dist. by Energique, Inc.

201 Apple Blvd

Woodbine, IA 51579 800.869.8078

PACKAGE LABEL DISPLAY:

ENERGIQUE

SINCE 1987

HOMEOPATHIC REMEDY

DERMA SCALE HP

1 fl. oz. (30 ml)